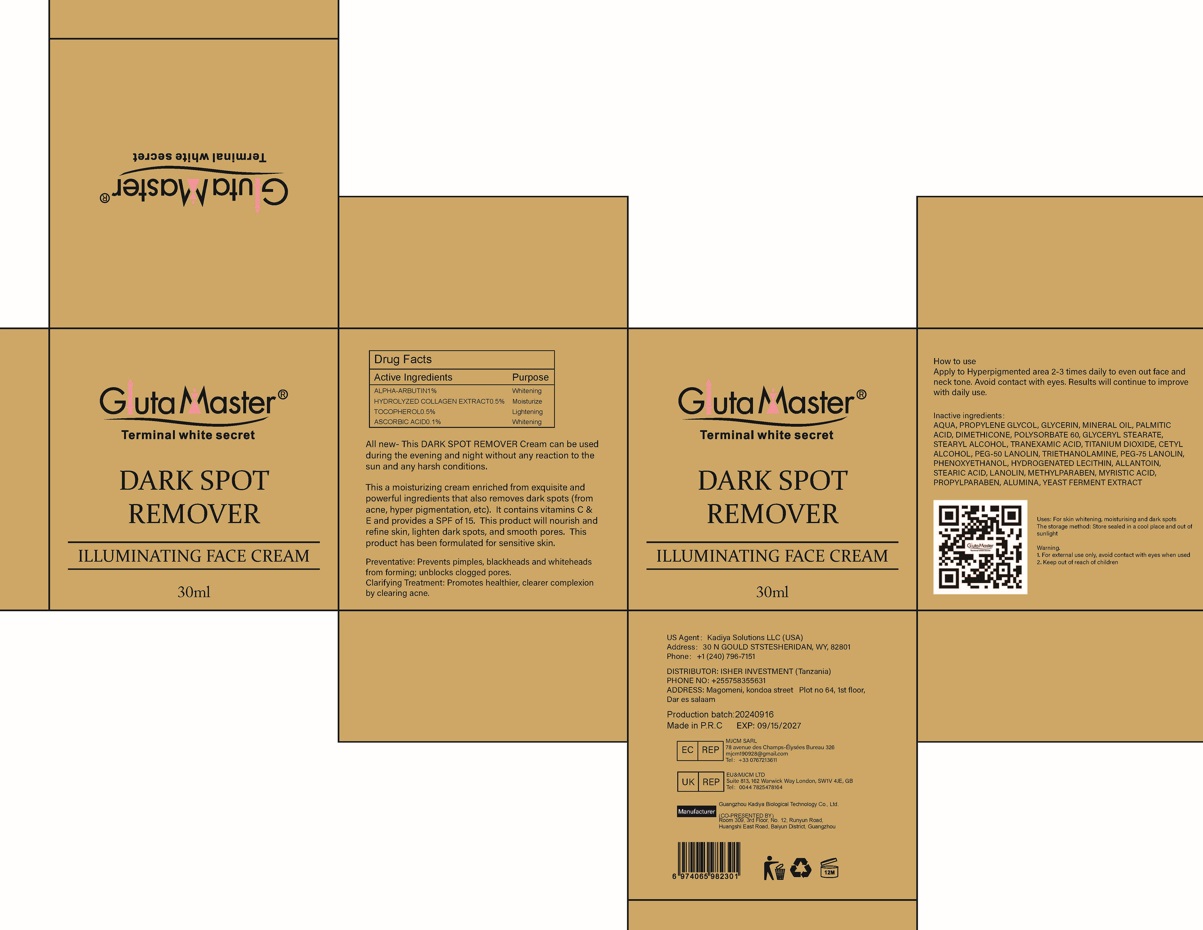 DRUG LABEL: DARKSPOTREMOVERILLUMINATINGFACECREAM
NDC: 84423-046 | Form: EMULSION
Manufacturer: Guangzhou Kadiya Biotechnology Co., Ltd.
Category: otc | Type: HUMAN OTC DRUG LABEL
Date: 20241217

ACTIVE INGREDIENTS: ALPHA-ARBUTIN 0.3 g/30 mL; TOCOPHEROL 0.015 g/30 mL; ASCORBIC ACID 0.03 g/30 mL
INACTIVE INGREDIENTS: PEG-75 LANOLIN; PROPYLPARABEN; TRANEXAMIC ACID; PEG-50 LANOLIN; MYRISTIC ACID; AQUA; CETYL ALCOHOL; METHYLPARABEN; PROPYLENE GLYCOL; PHENOXYETHANOL; STEARIC ACID; ALUMINA; LANOLIN; PALMITIC ACID; GLYCERYL STEARATE; STEARYL ALCOHOL; MINERAL OIL; DIMETHICONE 1000; TITANIUM DIOXIDE; TRIETHANOLAMINE; GLYCERIN; POLYSORBATE 60; ALLANTOIN

PURPOSE

For skin whitening, moisturising and dark spots

INACTIVE INGREDIENT

AQUA，PROPYLENE GLYCOL，GLYCERIN，MINERAL OIL，PALMITIC ACID，DIMETHICONE，POLYSORBATE 60，GLYCERYL STEARATE，STEARYL ALCOHOL，TRANEXAMIC ACID，TITANIUM DIOXIDE，CETYL ALCOHOL，PEG-50 LANOLIN，TRIETHANOLAMINE，PEG-75 LANOLIN，PHENOXYETHANOL，HYDROGENATED LECITHIN，ALLANTOIN，STEARIC ACID，LANOLIN，METHYLPARABEN，MYRISTIC ACID，PROPYLPARABEN，ALUMINA，YEAST FERMENT EXTRACT

WARNINGS

1、For external use only, avoid contact with eyes when used
2、Keep out of reach of children

INDICATIONS AND USAGE

Thie s mdieturizina croam onrichod fem avouieito and powertul ingredients that also removes dark spots (from acne. hvper pigmentation, etc). It contains vitamins C & E and provides a SPF of 15. This product will nourish and refine skin. linhten dark snots and smooth nores This product has been formulated for sensitive skin.

DOSAGE AND ADMINISTRATION

Apply to Hyperpigmented area 2-3 times daily to even out face and neck tone. Avoid contact with eyes. Results will continue to improve with daily use.

KEEP OUT OF REACH OF CHILDREN SECTION

ACTIVE INGREDIENT

ALPHA-ARBUTIN1%
HYDROLYZED COLLAGEN EXTRACT0.5%
TOCOPHEROL0.5%
ASCORBIC ACID0.1%

PACKAGE LABEL

Active Ingredients
ALPHA-ARBUTIN 1%
HYDROLYZED COLLAGEN EXTRACT 0.5%
TOCOPHEROL 0.5%
ASCORBIC ACID 0.1%

Uses：
For skin whitening, moisturising and dark spots

The storage method：
Store sealed in a cool place and out of sunlight

Warning.
1、For external use only, avoid contact with eyes when used
2、Keep out of reach of children

Inactive ingredients：
AQUA，PROPYLENE GLYCOL，GLYCERIN，MINERAL OIL，PALMITIC ACID，DIMETHICONE，POLYSORBATE 60，GLYCERYL STEARATE，STEARYL ALCOHOL，TRANEXAMIC ACID，TITANIUM DIOXIDE，CETYL ALCOHOL，PEG-50 LANOLIN，TRIETHANOLAMINE，PEG-75 LANOLIN，PHENOXYETHANOL，HYDROGENATED LECITHIN，ALLANTOIN，STEARIC ACID，LANOLIN，METHYLPARABEN，MYRISTIC ACID，PROPYLPARABEN，ALUMINA，YEAST FERMENT EXTRACT